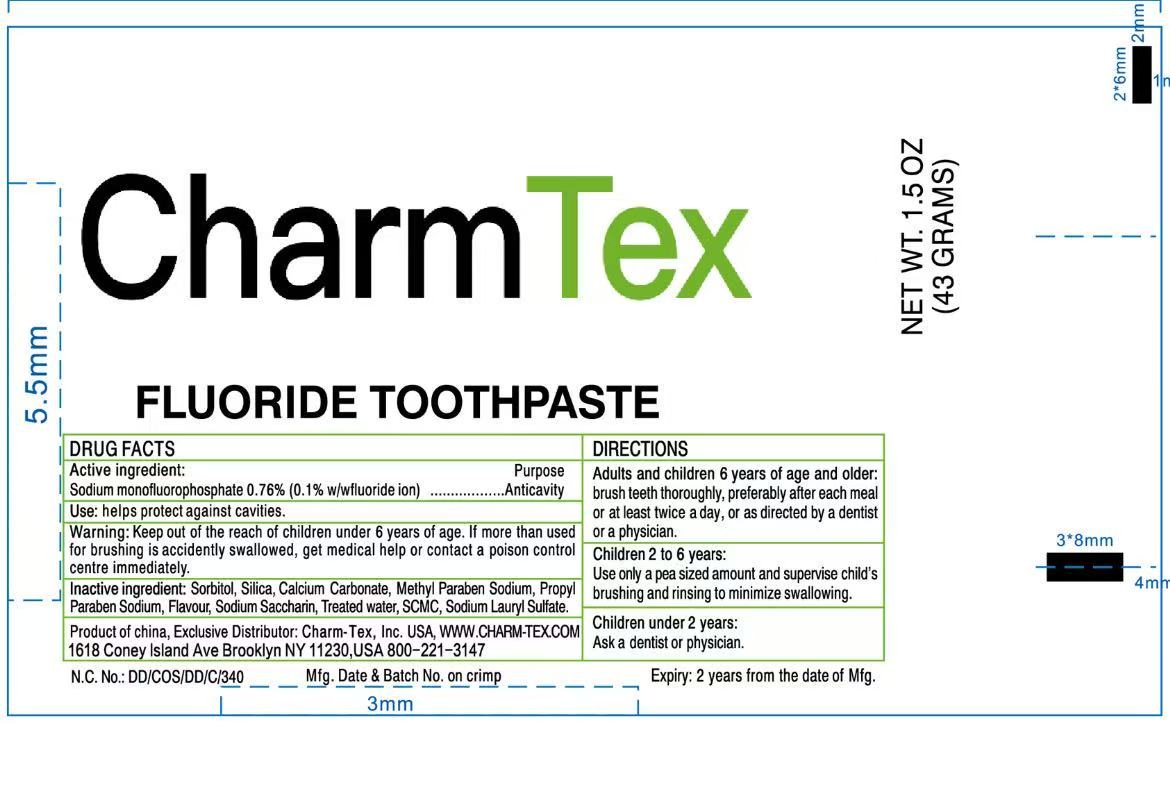 DRUG LABEL: Charm Tex FLUORIDE
NDC: 71035-001 | Form: PASTE, DENTIFRICE
Manufacturer: Yangzhou Hongshengding Chemical Co.,Ltd.
Category: otc | Type: HUMAN OTC DRUG LABEL
Date: 20250818

ACTIVE INGREDIENTS: SODIUM MONOFLUOROPHOSPHATE 0.1 g/100 g
INACTIVE INGREDIENTS: SACCHARIN SODIUM; SORBITOL; GLYCERIN; HYDRATED SILICA; SODIUM LAURYL SULFATE; CALCIUM CARBONATE; WATER; METHYLPARABEN SODIUM; PROPYLPARABEN SODIUM

71035-001 Tooth paste

Active Ingredient

SODIUM MONOFLUOROPHOSPHATE: 0.76% (0.1% Fluoride ion)

Purpose: Anticavity

Uses

Help protect against cavities.

Warnings

Keep out of the reach of children under 6 years of age. If more than used for brushing is accidently swallowed, get medical help or contact a Poison Control Center immediately.

Keep out of reach of children.

Directions

- Adults and children 6 years of age and older:Brush teeth thoroughly,preferably after each meal or at least twice a day,or as directed by a dentist or a physician.
- Children 2 to 6 years: Use only a pea sized amount and supervise children's brushing and rinsing to minimize swallowing
- Children under 2 years: Ask a dentist or physician

INACTIVE INGREDIENT

Sorbitol, Silica, Calcium Carbonate, Methylparaben Sodium, Propylparaben Sodium, Flavor, Sodium Saccharin, Water, SCMC, Sodium Lauryl Sulfate